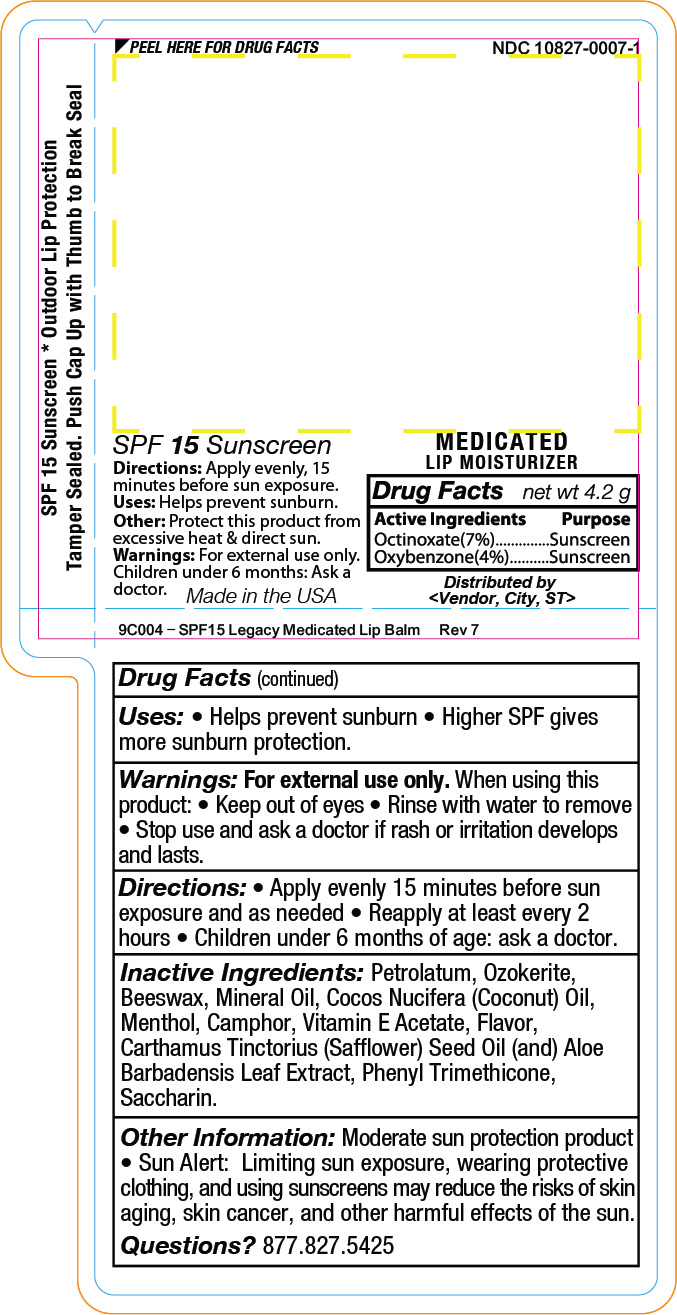 DRUG LABEL: YMLABS
NDC: 10827-0007 | Form: STICK
Manufacturer: Yusef Manufacturing Laboratories
Category: otc | Type: HUMAN OTC DRUG LABEL
Date: 20220124

ACTIVE INGREDIENTS: OXYBENZONE 0.168 g/4.2 g; OCTINOXATE 0.294 g/4.2 g
INACTIVE INGREDIENTS: WHITE WAX; COCONUT OIL; SUNFLOWER OIL; TOCOPHEROL; ALPHA-TOCOPHEROL ACETATE; SAFFLOWER OIL; ALOE VERA LEAF; CAMPHOR (NATURAL) 0.032 g/4.2 g; MENTHOL 0.084 g/4.2 g

YMlabs SPF15 Legacy Medicated Lip Balm

SPF 15 Sunscreen

Uses: Helps prevent sunburn.
Directions: Apply evenly, 15
minutes before sun exposure.
Other: Protect this product from
excessive heat & direct sun.
Warnings: For external use only.
Children under 6 months: Ask a
doctor.

<INSERT FLAVOR>

MEDICATED LIP MOISTURIZER

Drug Facts net wt 4.2g
Active Ingredients Purpose
Octinoxate (7%).............Sunscreen

Oxybenzone (4%)...........Sunscreen

Made in the USA

Distributed by
<Vendor, City, ST>

Drug Facts (continued)
Uses: • Helps prevent sunburn • Higher SPF gives
more sunburn protection.

Warnings: For external use only. When using this
product: • Keep out of eyes • Rinse with water to remove
• Stop use and ask a doctor if rash or irritation develops
and lasts.

INSTRUCTIONS FOR USE

Directions: • Apply evenly 15 minutes before sun
exposure and as needed • Reapply at least every 2
hours • Children under 6 months of age: ask a doctor.

Inactive Ingredients: Beeswax, Cocos Nucifera
(Coconut) Oil, Helianthus Annuus (Sunflower) Seed Oil,
Tocopherol, Tocopheryl Acetate, Carthamus Tinctorius
(Safflower) Seed Oil (and) Aloe Barbadenis Leaf Extract.

Other Information: Moderate sun protection product
• Sun Alert: Limiting sun exposure, wearing protective
clothing, and using sunscreens may reduce the risks of
skin aging, skin cancer, and other harmful effects of the
sun.
Questions? 877.827.5425